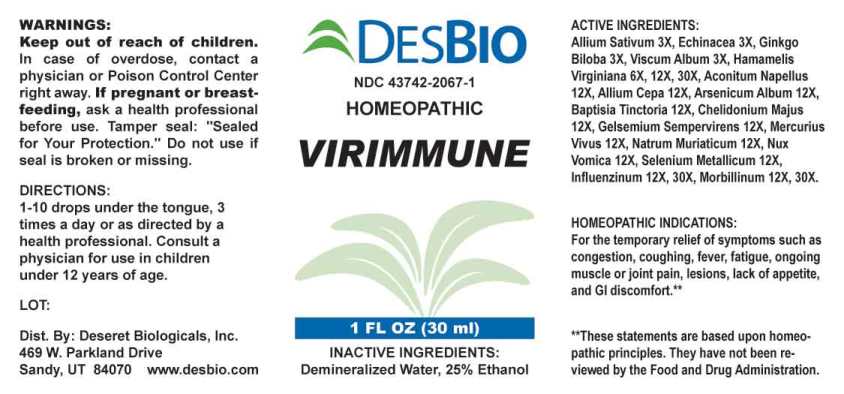 DRUG LABEL: Virimmune
NDC: 43742-2067 | Form: LIQUID
Manufacturer: Deseret Biologicals, Inc.
Category: homeopathic | Type: HUMAN OTC DRUG LABEL
Date: 20240305

ACTIVE INGREDIENTS: GARLIC 3 [hp_X]/1 mL; ECHINACEA ANGUSTIFOLIA WHOLE 3 [hp_X]/1 mL; GINKGO 3 [hp_X]/1 mL; VISCUM ALBUM FRUITING TOP 3 [hp_X]/1 mL; HAMAMELIS VIRGINIANA ROOT BARK/STEM BARK 6 [hp_X]/1 mL; ACONITUM NAPELLUS WHOLE 12 [hp_X]/1 mL; ONION 12 [hp_X]/1 mL; ARSENIC TRIOXIDE 12 [hp_X]/1 mL; BAPTISIA TINCTORIA ROOT 12 [hp_X]/1 mL; CHELIDONIUM MAJUS WHOLE 12 [hp_X]/1 mL; GELSEMIUM SEMPERVIRENS ROOT 12 [hp_X]/1 mL; MERCURY 12 [hp_X]/1 mL; SODIUM CHLORIDE 12 [hp_X]/1 mL; STRYCHNOS NUX-VOMICA SEED 12 [hp_X]/1 mL; SELENIUM 12 [hp_X]/1 mL; INFLUENZA A VIRUS A/VICTORIA/2570/2019 IVR-215 (H1N1) ANTIGEN (UV, FORMALDEHYDE INACTIVATED) 12 [hp_X]/1 mL; INFLUENZA A VIRUS A/DARWIN/9/2021 IVR-228 (H3N2) ANTIGEN (UV, FORMALDEHYDE INACTIVATED) 12 [hp_X]/1 mL; INFLUENZA B VIRUS B/AUSTRIA/1359417/2021 BVR-26 ANTIGEN (UV, FORMALDEHYDE INACTIVATED) 12 [hp_X]/1 mL; INFLUENZA B VIRUS B/PHUKET/3073/2013 ANTIGEN (UV, FORMALDEHYDE INACTIVATED) 12 [hp_X]/1 mL; MEASLES VIRUS 12 [hp_X]/1 mL
INACTIVE INGREDIENTS: WATER; ALCOHOL

DRUG FACTS:

ACTIVE INGREDIENT:

Allium Sativum 3X, Echinacea (Angustifolia) 3X, Ginkgo Biloba 3X, Viscum Album 3X, Hamamelis Virginiana 6X, 12X, 30X, Aconitum Napellus 12X, Allium Cepa 12X, Arsenicum Album 12X, Baptisia Tinctoria 12X, Chelidonium Majus 12X, Gelsemium Sempervirens 12X, Mercurius Vivus 12X, Natrum Muriaticum 12X, Nux Vomica 12X, Selenium Metallicum 12X, Influenzinum (2022-2023) 12X, 30X, Morbillinum 12X, 30X.

PURPOSES:

For the temporary relief of the symptoms such as congestion, coughing, fever, fatigue, ongoing muscle or joint pain, lesions, lack of appetite, and GI discomfort.**

**These statements are based upon homeopathic principles. They have not been reviewed by the Food and Drug Administration.

USES:

For the temporary relief of the symptoms such as congestion, coughing, fever, fatigue, ongoing muscle or joint pain, lesions, lack of appetite, and GI discomfort.**

**These statements are based upon homeopathic principles. They have not been reviewed by the Food and Drug Administration.

WARNINGS:

Keep out of reach of children. In case of overdose, contact a physician or Poison Control Center right away.

If pregnant or breast-feeding, ask a health professional before use.

Tamper seal: "Sealed for Your Protection." Do not use if seal is broken or missing.

Keep out of reach of children. In case of overdose, contact a physician or Poison Control Center right away.

DIRECTIONS:

1-10 drops under the tongue, 3 times a day or as directed by a health professional. Consult a physician for use in children under 12 years of age.

INACTIVE INGREDIENTS:

Demineralized Water, 25% Ethanol

QUESTIONS:

Dist. By: Deseret Biologicals, Inc.
469 W. Parkland Drive
Sandy, UT 84070 www.desbio.com

PACKAGE LABEL DISPLAY:

DESBIO

NDC 43742-2067-1

HOMEOPATHIC

VIRIMMUNE

1 FL OZ (30 ml)